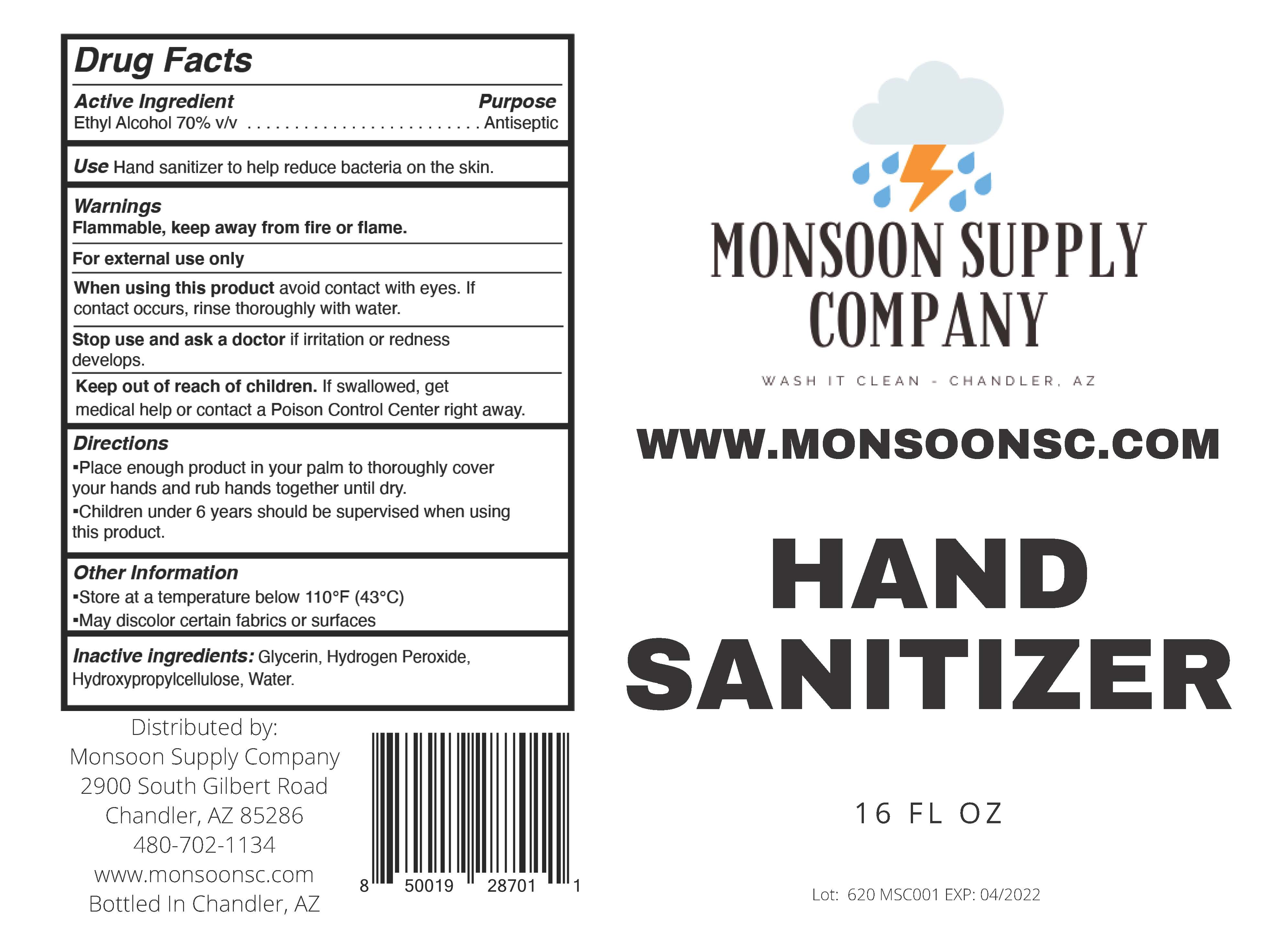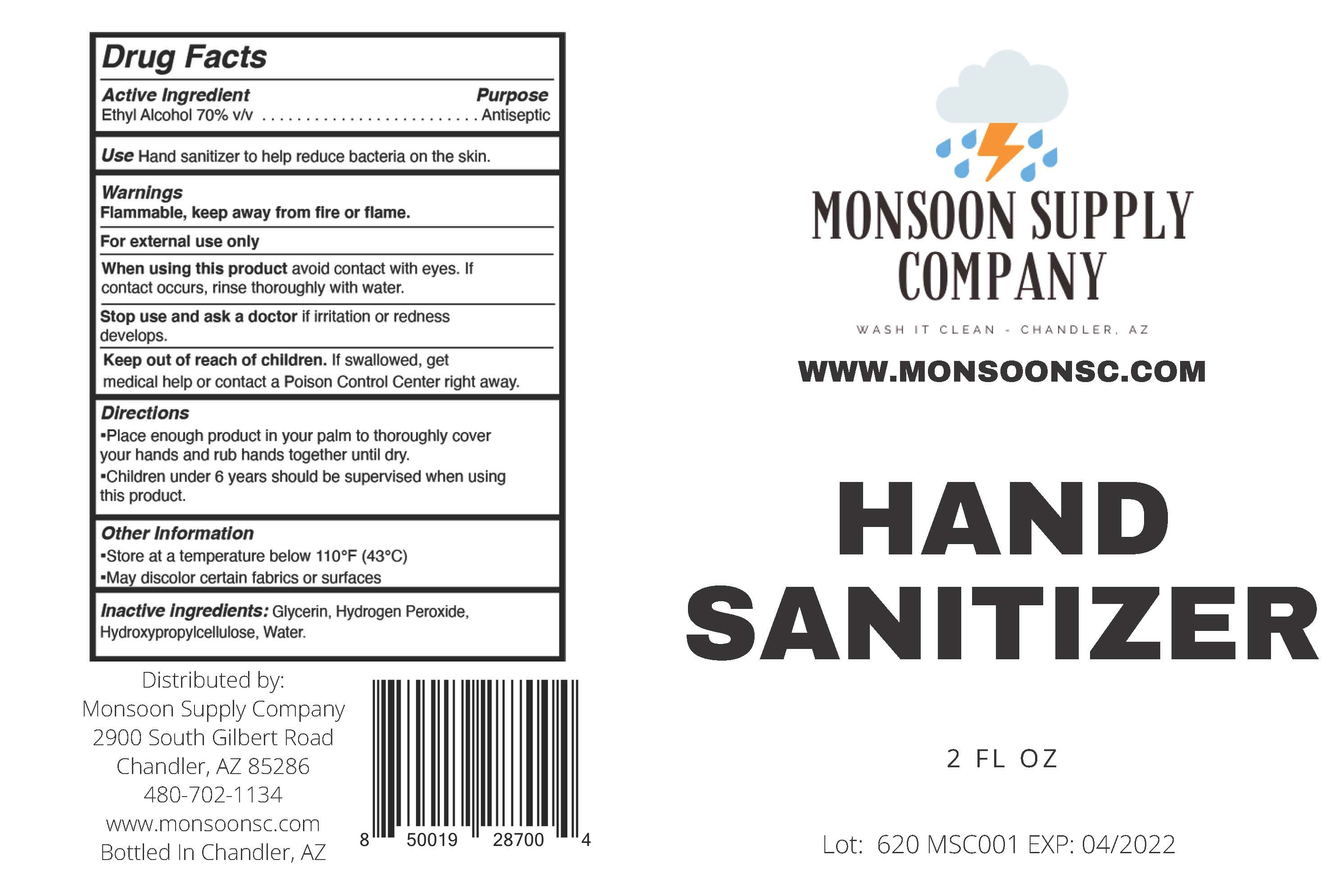 DRUG LABEL: Hand Sanitizer
NDC: 78948-648 | Form: GEL
Manufacturer: Ko-pack Inc
Category: otc | Type: HUMAN OTC DRUG LABEL
Date: 20200702

ACTIVE INGREDIENTS: ALCOHOL 70 mL/100 mL
INACTIVE INGREDIENTS: GLYCERIN; HYDROGEN PEROXIDE; WATER; HYDROXYETHYL CELLULOSE (4000 MPA.S AT 1%)

Monsoon Supply Company Hand Sanitizers

Active Ingredient(s)

Ethyl Alcohol 70% v/v. Purpose: Antiseptic

Purpose

Antiseptic

Use

Hand Sanitizer to help reduce bacteria on the skin

Warnings

Flammable, keep away from fire or flame

For external use only.

When using this product avoid contact with eyes. If contact occurs, rinse thoroughly with water.
Stop use and ask a doctor if irritation or redness develops.
Keep out of reach of children. If swallowed, get medical help or contact a Poison Control Center right away.

Stop use and ask a doctor if irritation or redness develops.

Keep out of reach of children. If swallowed, get medical help or contact a Poison Control Center right away.

Directions

- Place enough product in your palm to thoroughly cover your hands and rub hands together until dry.
- Children under 6 years should be supervised when using this product.

Other information

- Store at a temperature below 110 F (43 C)
- May discolor certain fabrics or surfaces

Inactive ingredients

Glycerin, Hydrogen Peroxide, Hydroxypropylcellulose, Water

Package Label - Principal Display Panel

59 mL NDC: 78948-648-02

473 mL NDC: 78948-648-16